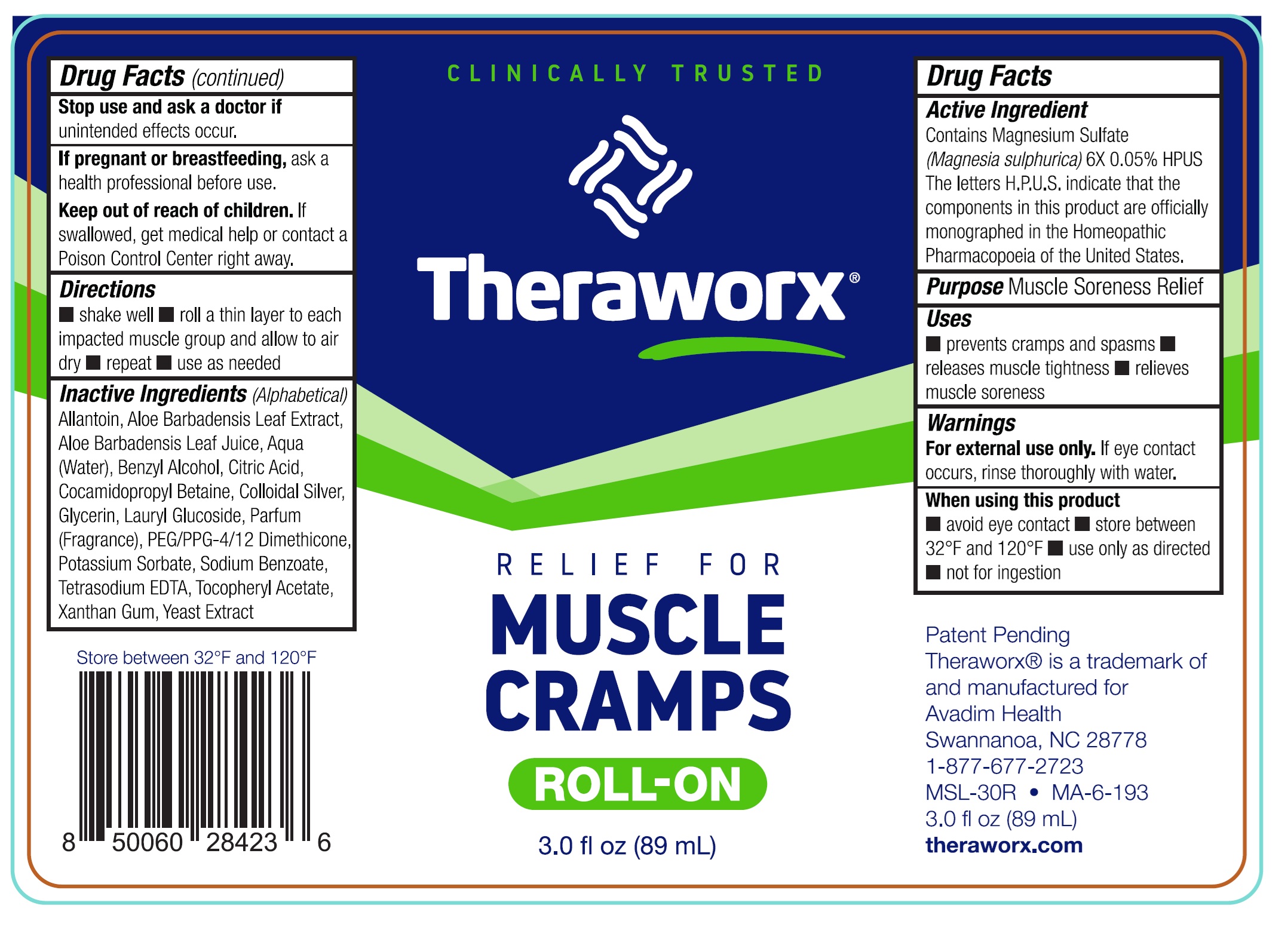 DRUG LABEL: Theraworx Relief for Muscle Cramps Roll-On
NDC: 61594-046 | Form: AEROSOL
Manufacturer: AVADIM HOLDINGS, INC.
Category: homeopathic | Type: HUMAN OTC DRUG LABEL
Date: 20240926

ACTIVE INGREDIENTS: MAGNESIUM SULFATE, UNSPECIFIED FORM 6 [hp_X]/1 mL
INACTIVE INGREDIENTS: ALLANTOIN; ALOE VERA LEAF; WATER; BENZYL ALCOHOL; CITRIC ACID MONOHYDRATE; COCAMIDOPROPYL BETAINE; SILVER; GLYCERIN; LAURYL GLUCOSIDE; PEG/PPG-4/12 DIMETHICONE; POTASSIUM SORBATE; SODIUM BENZOATE; EDETATE SODIUM; .ALPHA.-TOCOPHEROL ACETATE; XANTHAN GUM; YEAST, UNSPECIFIED

Theraworx Relief for Muscle Cramps Roll-On

Active Ingredient

Contains Magnesium Sulfate (Magnesia sulphurica)6X 0.05% HPUS The letters H.P.U.S. indicate that the componets in this product are officially monograped in the Homepathic Pharmacopoeia of the United States.

Purpose

Muscle Soreness Relief

Uses

- prevents cramps and spasms
- releases muscle tightness
- relieves muscle soreness

Warnings

For external use only.If eye contact occurs, rinse thoroughly with water.

When using this product

- avoid eye contact
- store between 32°F and 120°F
- use only as directed
- not for ingestion

Stop use and ask a doctor if

unintended effects occur.

If pregnant or breastfeeding,

ask a health professional before use.

Keep out of reach of children.

If swallowed, get medical help or contact a Poison Control Center right away.

Directions

- shake well
- roll a thin layer to each impacted muscle group and allow to air dry
- repeat
- use as needed

Inactive Ingredients

(Alphabetical)Allantoin, Aloe Barbadensis Leaf Extract, Aloe Barbadensis Leaf Juice, Aqua (Water), Benzyl Alcohol, Citric Acid, Cocamidopropyl Betaine, Colloidal Silver, Glycerin, Lauryl Glucoside, Parfum (Fragrance), PEG/PPG-4/12 Dimethicone, Potassium Sorbate, Sodium Benzoate, Tetrasodium EDTA, Tocopheryl Acetate, Xanthan Gum, Yeast Extract

Store between 32°F and 120°F